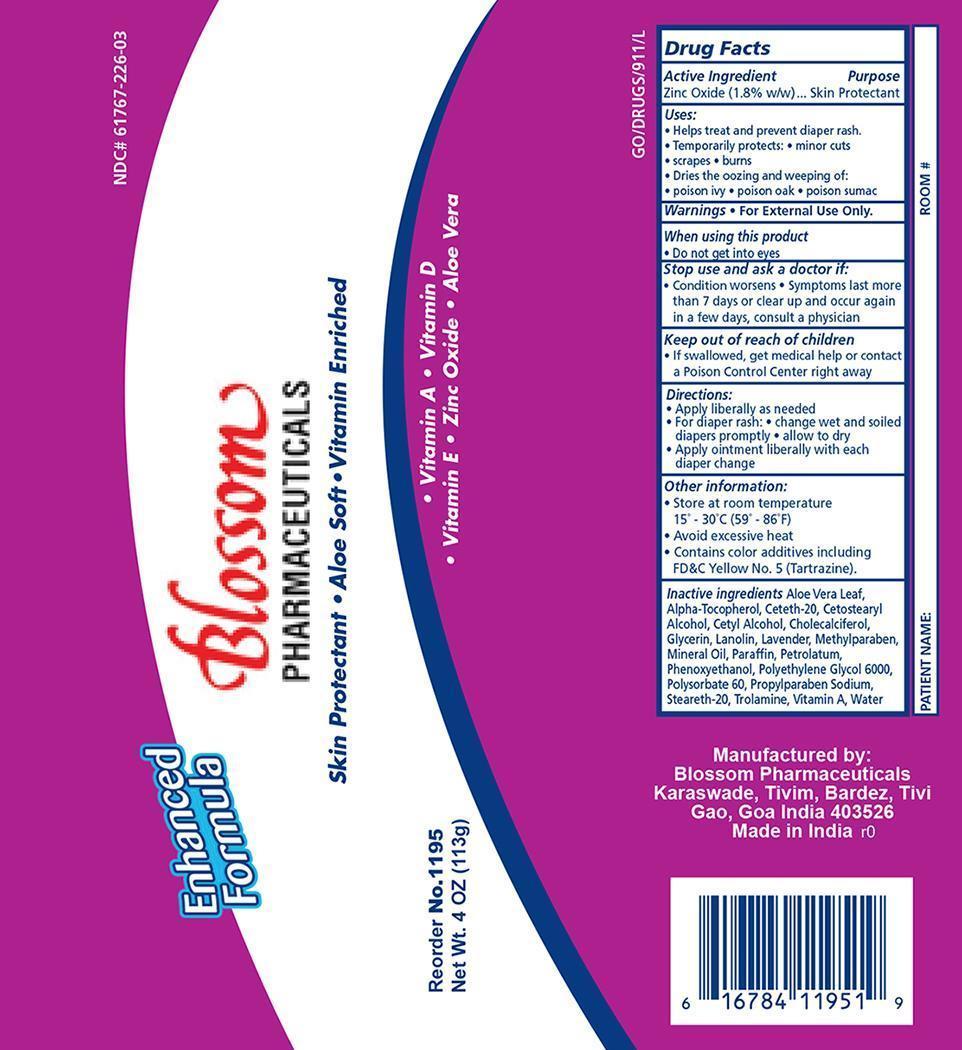 DRUG LABEL: Dyna1195
NDC: 61767-226 | Form: OINTMENT
Manufacturer: Blossom Pharmaceuticals
Category: otc | Type: HUMAN OTC DRUG LABEL
Date: 20141023

ACTIVE INGREDIENTS: ZINC OXIDE 1.8 g/100 g
INACTIVE INGREDIENTS: LANOLIN; CETETH-20; MINERAL OIL; METHYLPARABEN; PROPYLPARABEN; GLYCERIN; CETYL ALCOHOL; CETOSTEARYL ALCOHOL; CHOLECALCIFEROL; VITAMIN A; ALPHA-TOCOPHEROL; ALOE VERA LEAF; PETROLATUM; TROLAMINE; WATER

Dyna1195 Ointment

Active Ingredient Purpose

Zinc Oxide (1.8% w/w) Skin Protectant

Purpose:

- Helps treat and prevent diaper rash
- Temporarily protects
- minor cuts
- scrapes and
- burns
- dries the oozing and weeping of
- poison ivy
- poison oak
- poison sumac

Warnings:

For External Use Only.

When using this product:

Do not get in eyes.

Stop use and ask a doctor if:

- condition worsens
- symptoms last more than 7 days or clear up and occur again in a few days, consult a physician

Keep out of reach of children.

If swallowed, get medical help or contact a Poison Control Center right away.

Dosage and Administration:

For skin protectant:

- Apply liberally as needed

For diaper Rash:

- change wet and soiled diapers promptly
- allow to dry
- apply ointment liberally with each diaper change

Other information:

- Store at room temperature
- avoid excessive heat
- contains color additives including FDC yellow # 5 (Tartrazine)

INDICATIONS AND USAGE

Indications: For use as a general skin protectant and diaper rash.

Inactive ingredients:

Aloe Vera Leaf, Alpha-Tocopherol, Ceteth-20, Cetostearyl Alcohol, Cetyl Alcohol, Cholecalciferol, Glycerin, Lanolin, Lavender perfume, Methylparaben, Mineral Oil, Petrolatum, Propylparaben, Trolamine, Vitamin A, Water

Principal Display Panel

Dyna1195 Skin Protectant

Dyna1195.jpg